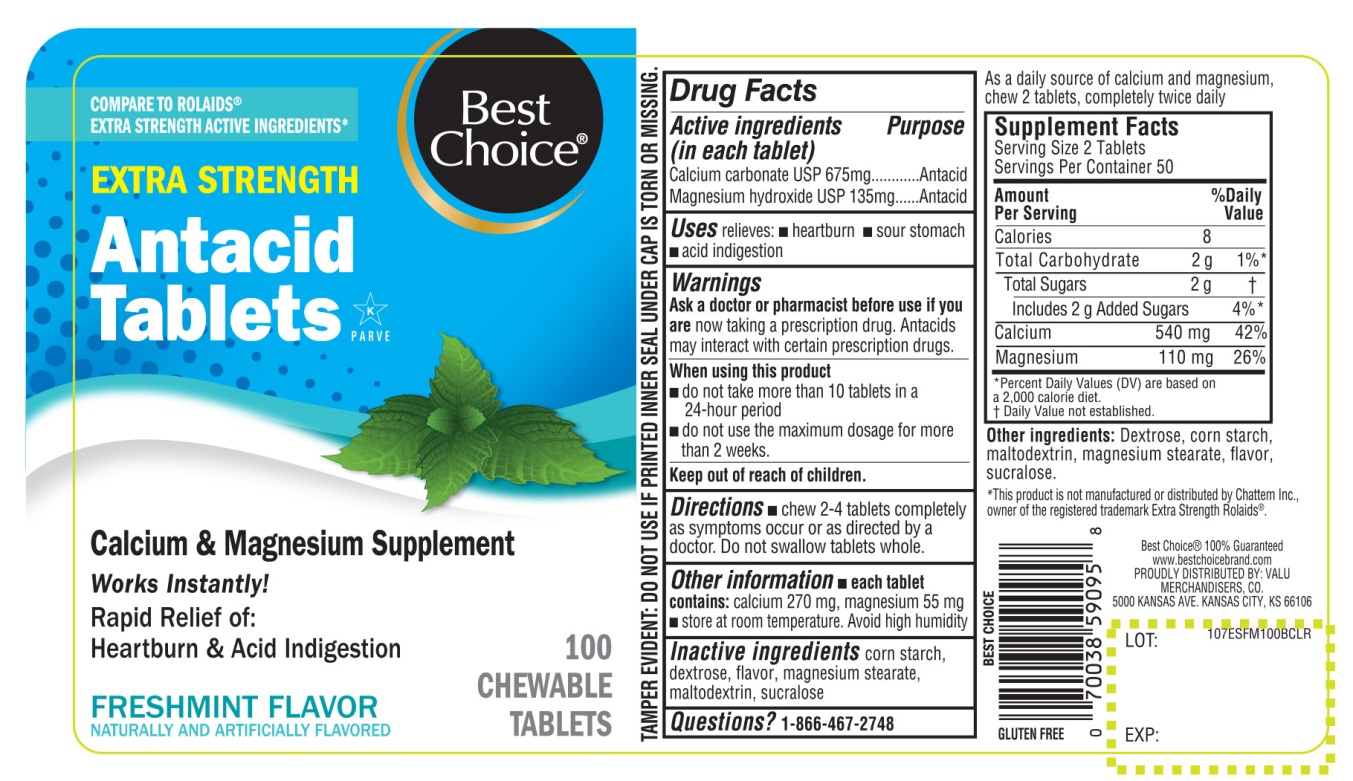 DRUG LABEL: Best Choice

NDC: 63941-071 | Form: TABLET, CHEWABLE
Manufacturer: BEST CHOICE (VALU MERCHANDISERS COMPANY)
Category: otc | Type: HUMAN OTC DRUG LABEL
Date: 20250716

ACTIVE INGREDIENTS: CALCIUM CARBONATE 675 mg/1 1; MAGNESIUM HYDROXIDE 135 mg/1 1
INACTIVE INGREDIENTS: STARCH, CORN; DEXTROSE, UNSPECIFIED FORM; MAGNESIUM STEARATE; MALTODEXTRIN; SUCRALOSE

Best Choice®Extra Strength Antacid Tablets Freshmint Flavor

Drug Facts

Active ingredients(in each tablet)

Calcium Carbonate USP 675 mg
Magnesium hydroxide USP 135 mg

Purpose

Antacid

Antacid

Uses

relieves:

- heartburn
- sour stomach
- acid indigestion

Warnings

Ask a doctor or pharmacist before use if you are

now taking a prescription drug. Antacids may interact with certain prescription drugs.

When using this product

- do not take more than 10 tablets in a 24-hour period
- do not use the maximum dosage for more than 2 weeks.

Directions

- chew 2-4 tablets as symptoms occur or as directed by a doctor.

Other information

- each tablet contains:calcium 270 mg, magnesium 55 mg
- store at room temperature
- Avoid high humidity.

As a daily source of calcium and magnesium, chew 2 tablets twice daily

Supplement Facts

Serving Size: 2 Tablets

Servings Per Container: 50

Amount Per Serving | % Daily Value
Calories | 8
Total Carbohydrate | 2g 1%
Total Sugars; Includes 2g Added Sugars | 2g †; 4% *
Calcium 540 mg | 42%
Magnesium 100 mg | 26%

*Percent Daily Values (DV) are based on a 2,000 calories diet.

†Daily Value not established.

Inactive ingredients

corn starch, dextrose, flavor, magnesium stearate, maltodextrin, sucralose.

Questions or comment?

1-866-467-2748

PRINCIPAL DISPLAY PANEL

Best Choice®

NDC# 63941-071-10

COMPARE TO ROLAIDS® EXTRA STRENGTH ACTIVE INGREDIENTS*

EXTRA STRENGTH

Antacid Tablets

Calcium & Magnesium Supplement

Works Instantly!

Rapid Relief of:

Heartburn & Acid Indigestion

FRESHMINT FLAVOR

NATURALLY AND ARTIFICIALLY FLAVORED

100 CHEWABLE TABLETS

GLUTEN FREE

TAMPER EVIDENT: DO NOT USE IF PRINTED SEAL UNDER CAP IS TORN OR MISSING

*This product is not manufactured or distributed by Chattem Inc., owner of the registered trademark Extra Strength Rolaids®

Best Choice® 100% Guaranteed

www.bestchoicebrand.com

PROUDLY DISTRIBUTED BY: VALU MERCHANDISERS, CO.

500 KANSAS AVE. KANSAS CITY, KS 66106